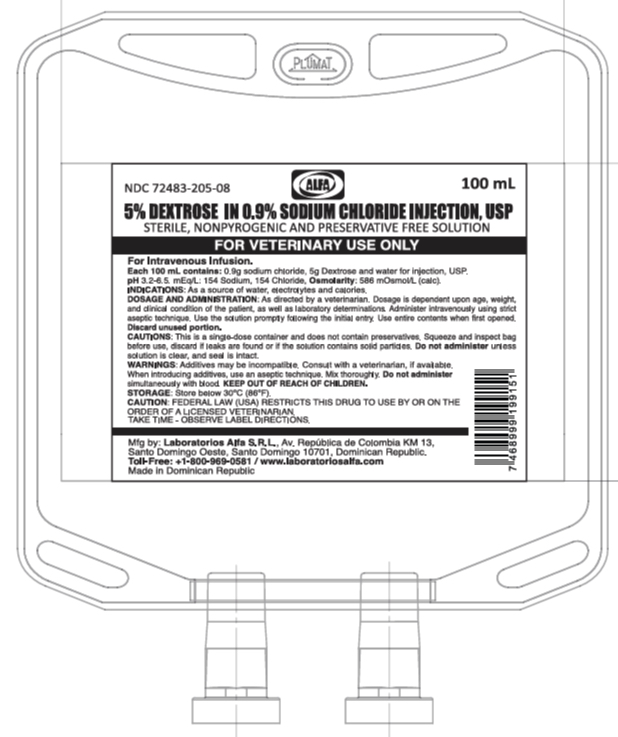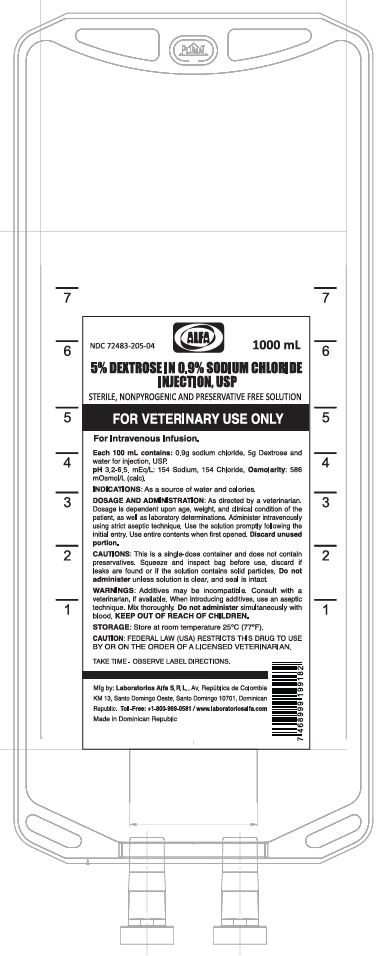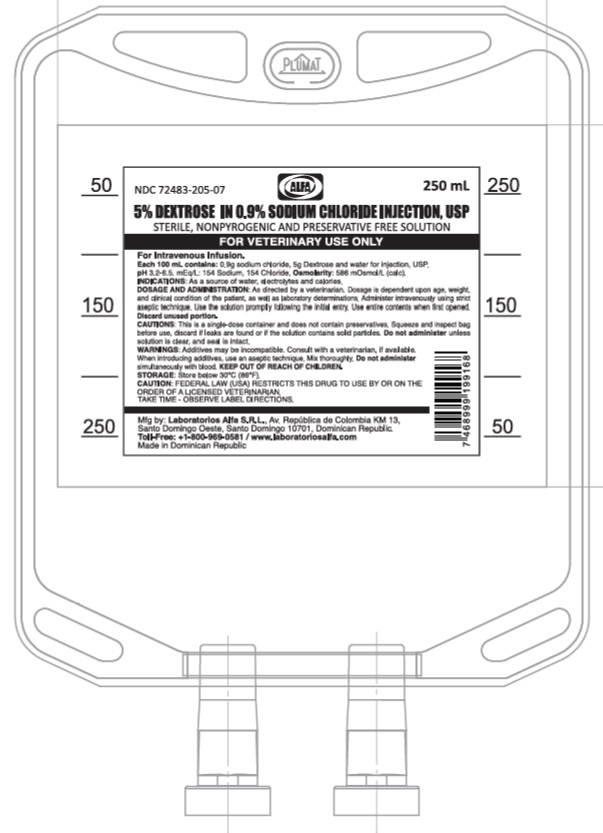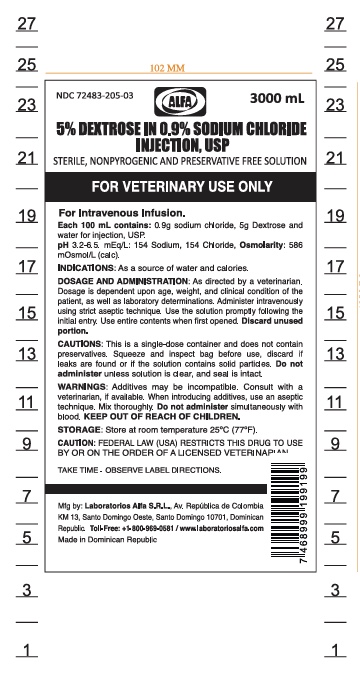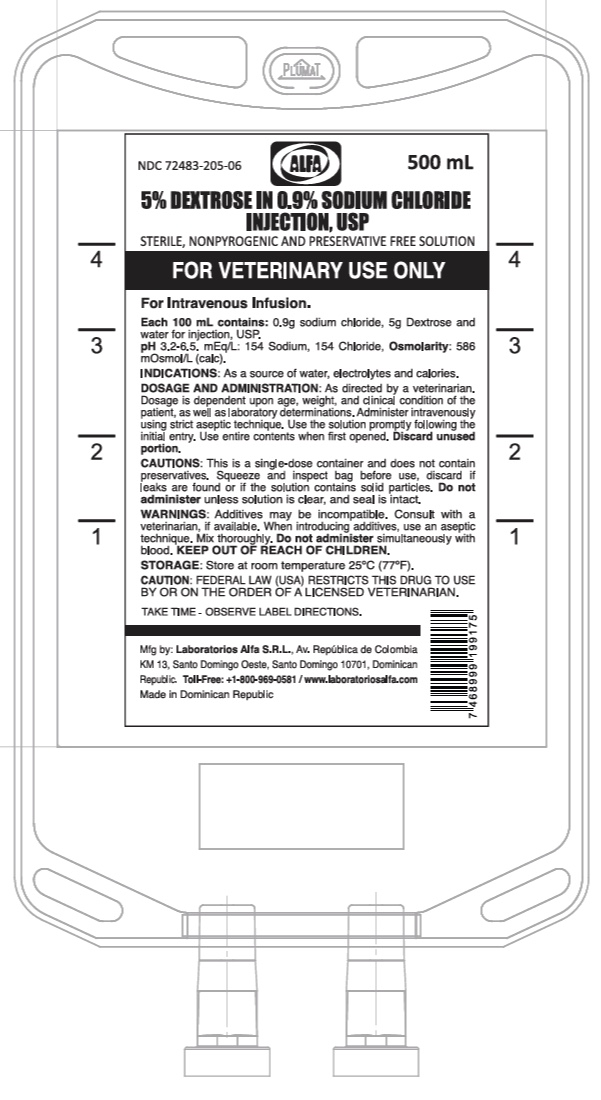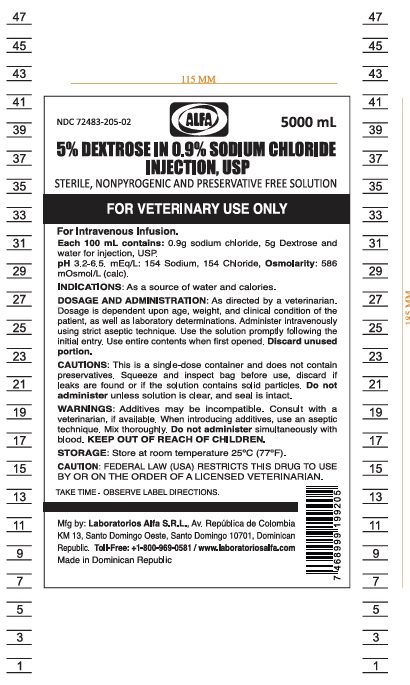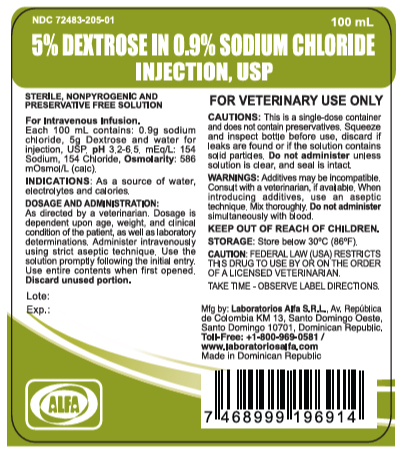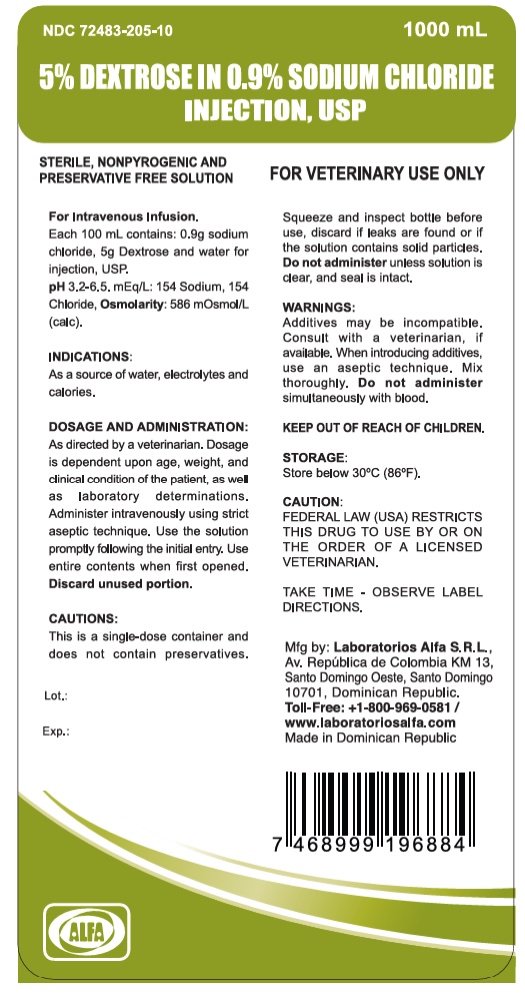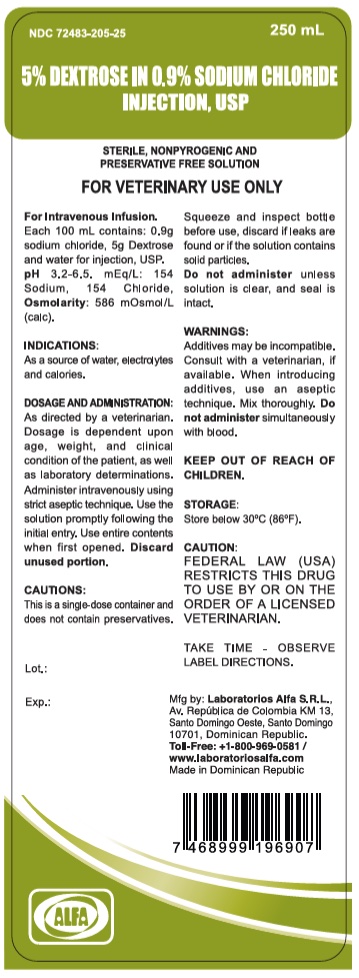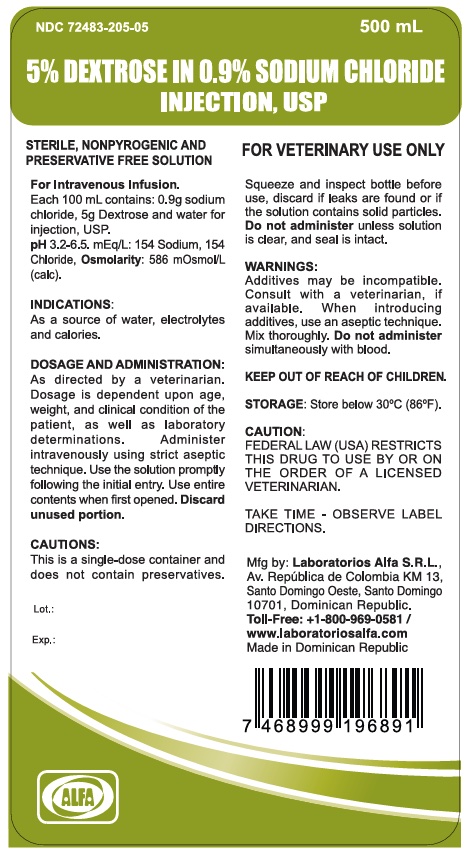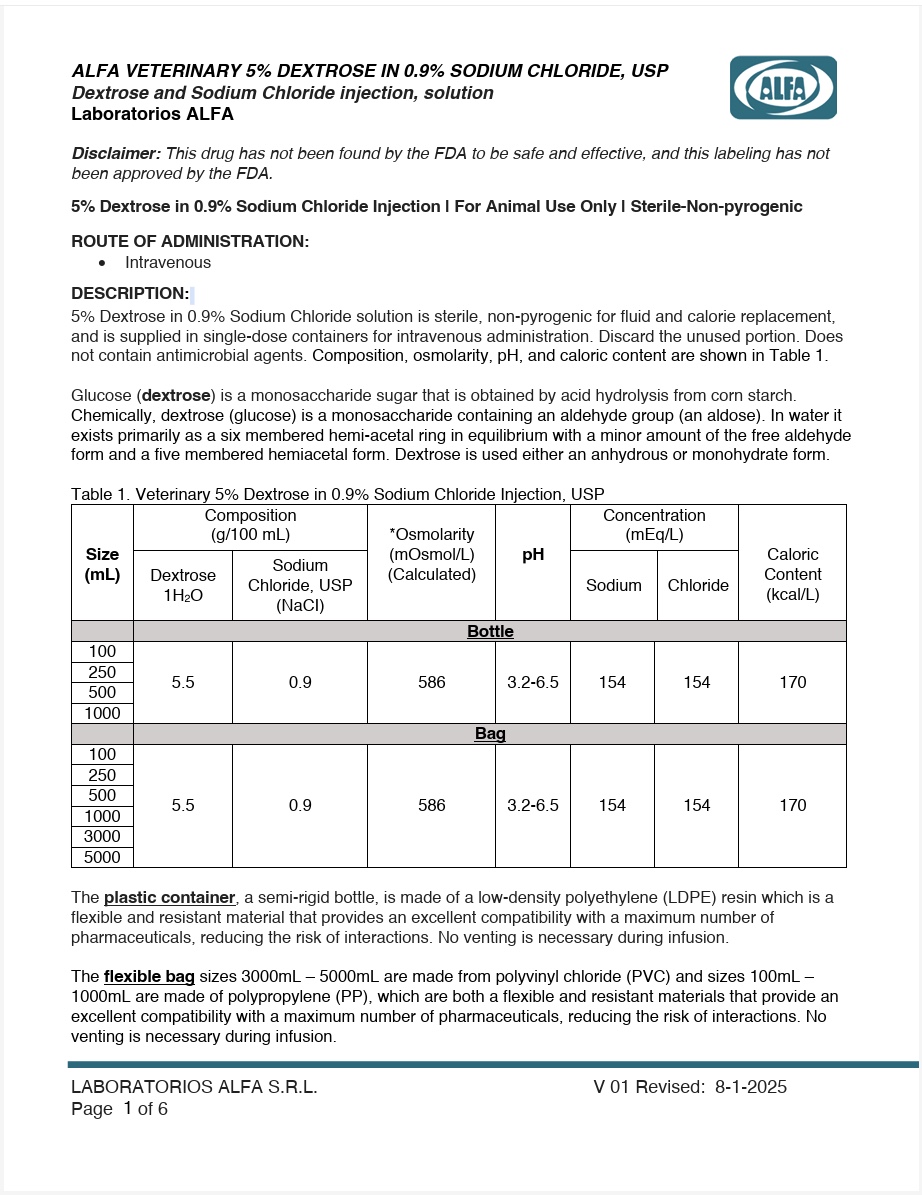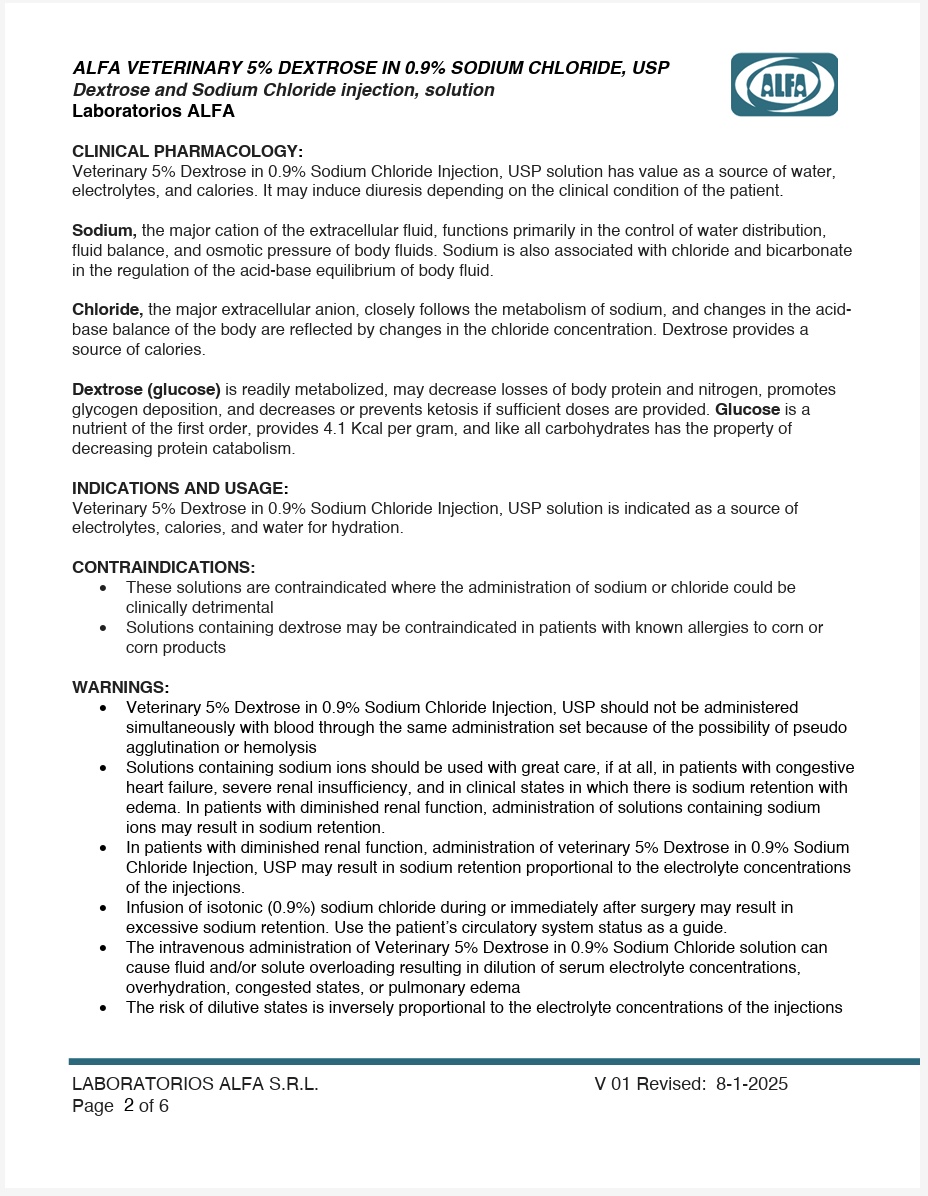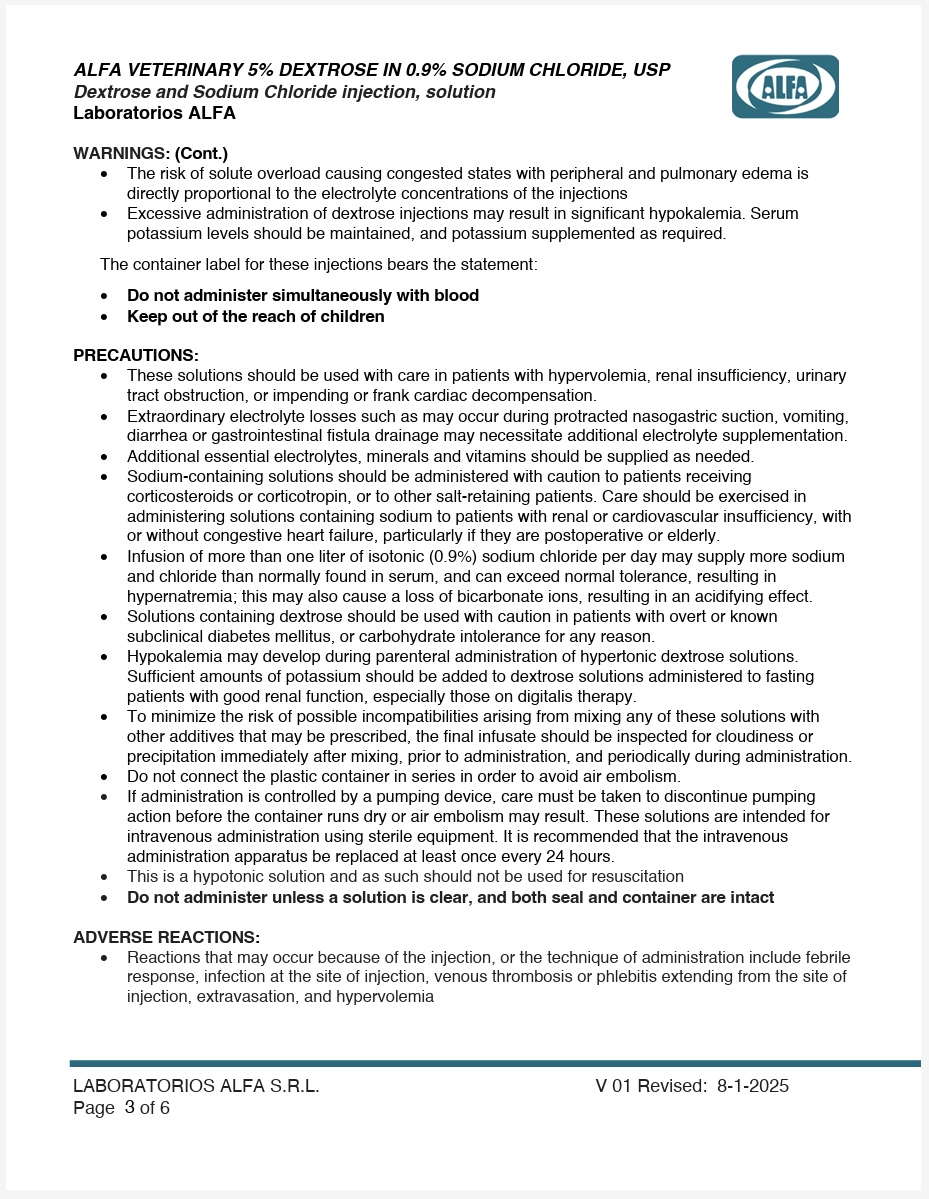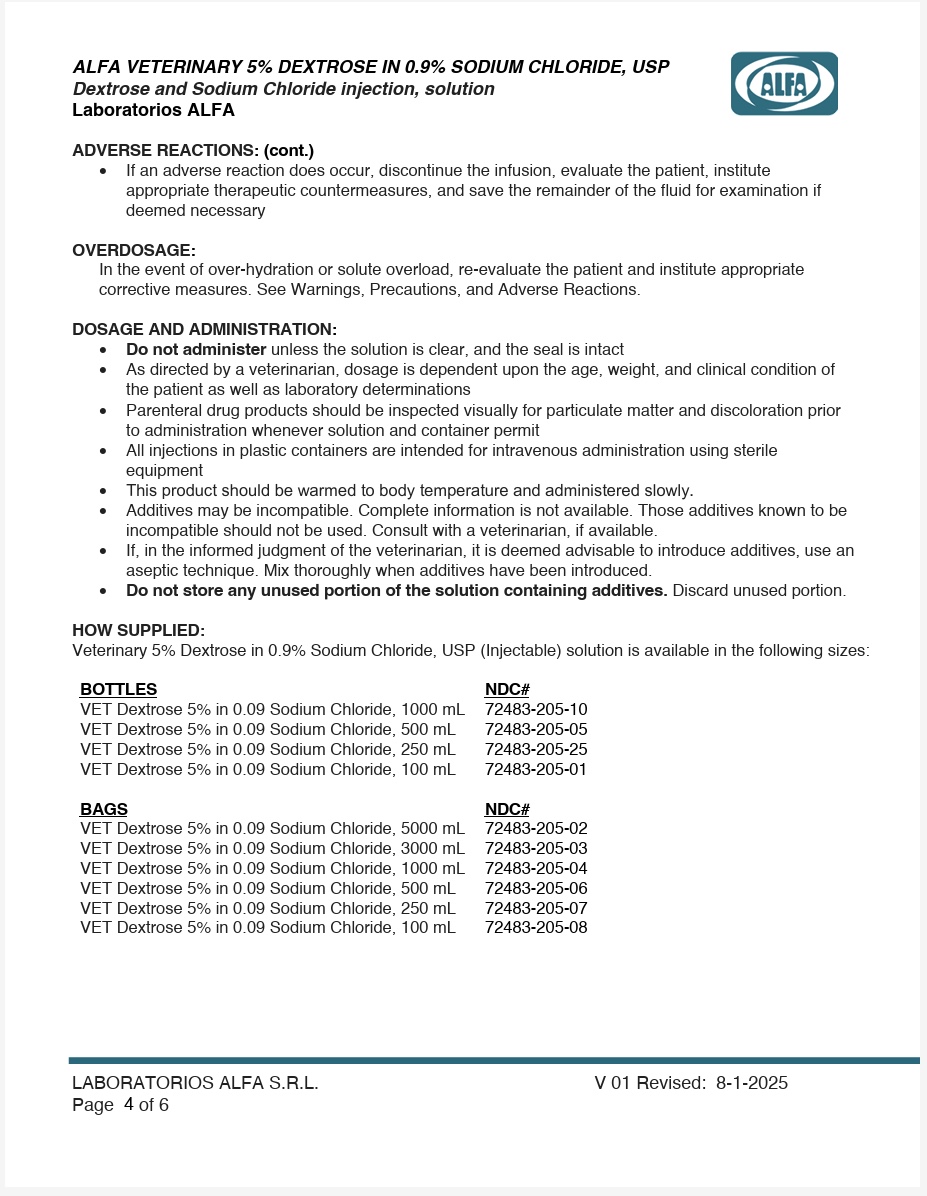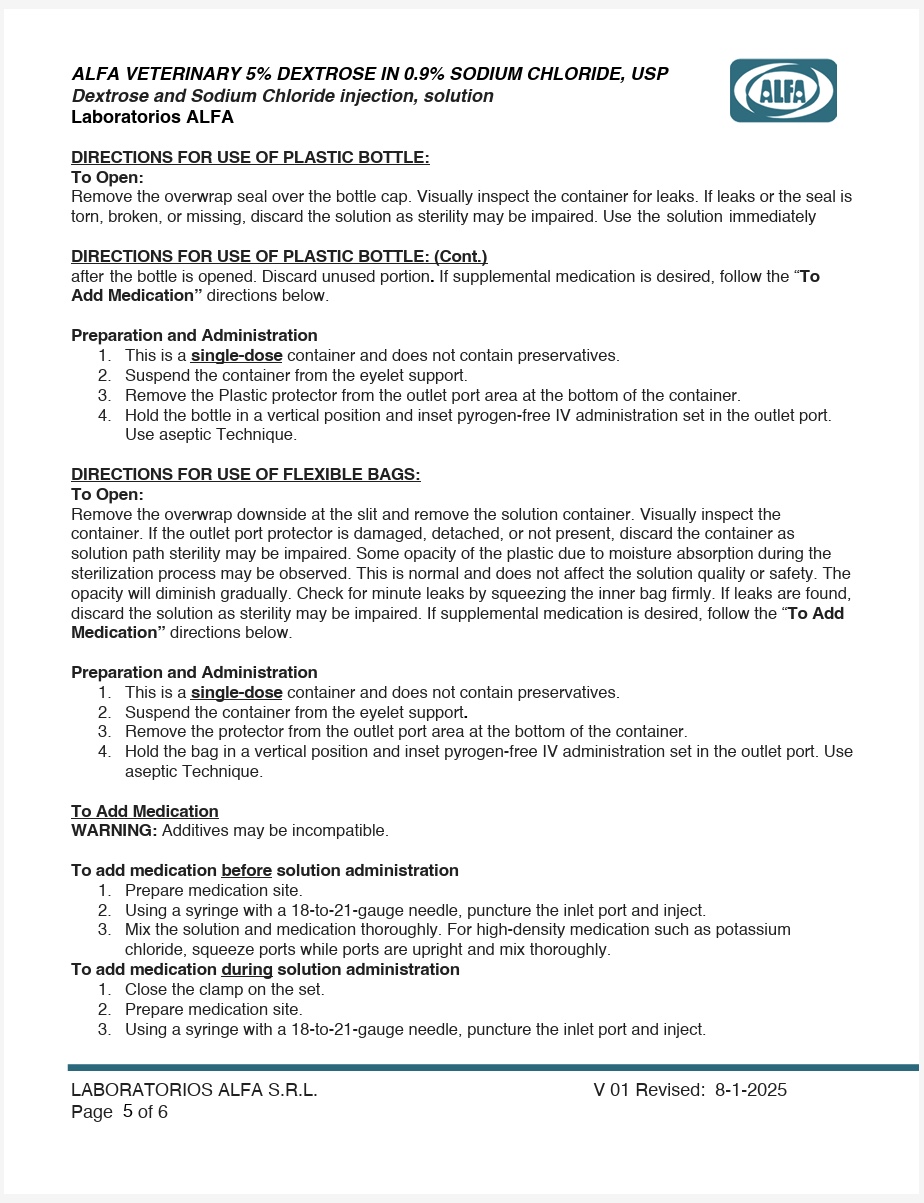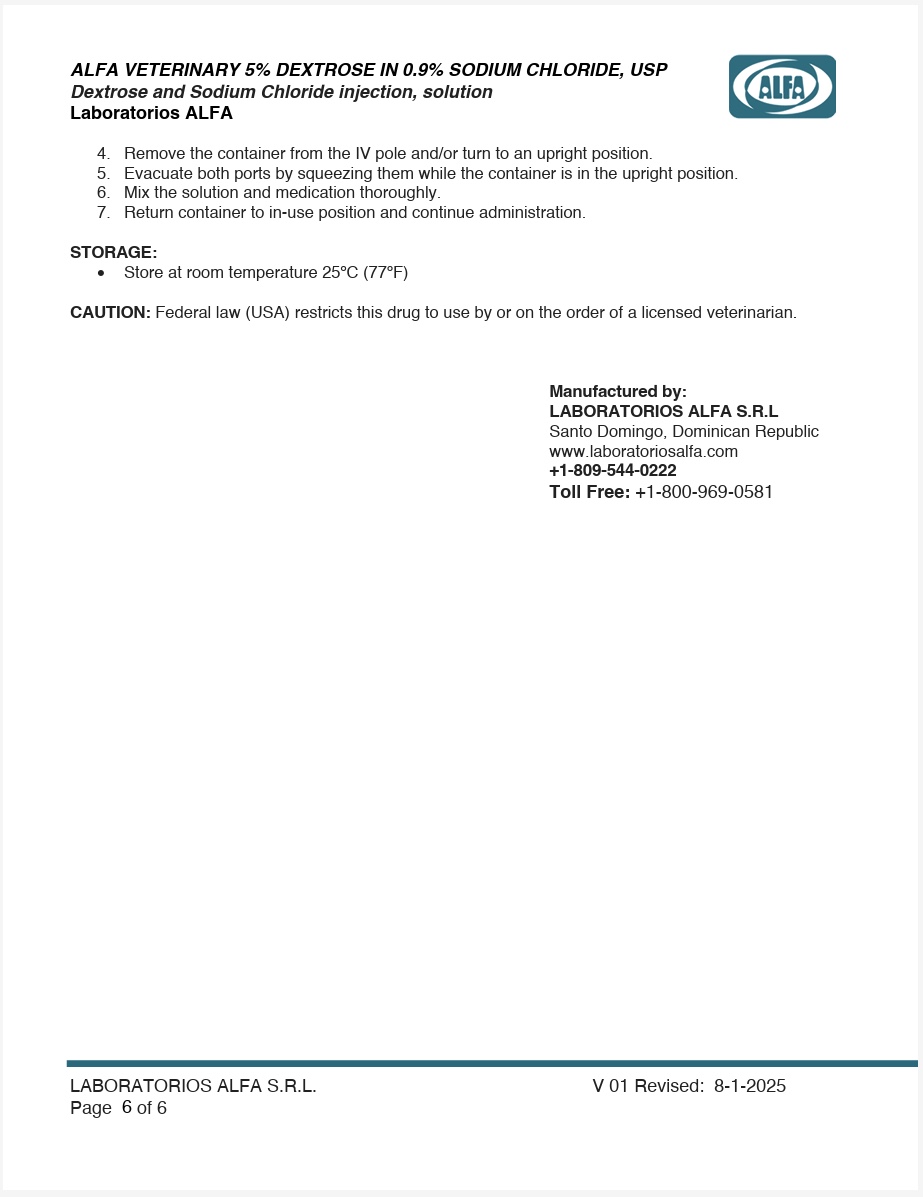 DRUG LABEL: Alfa Veterinary Dextrose and Sodium Chloride
NDC: 72483-205 | Form: INJECTION, SOLUTION
Manufacturer: Laboratorios Alfa SRL
Category: animal | Type: PRESCRIPTION ANIMAL DRUG LABEL
Date: 20250813

ACTIVE INGREDIENTS: DEXTROSE MONOHYDRATE 5.5 g/100 mL; SODIUM CHLORIDE 900 mg/100 mL
INACTIVE INGREDIENTS: WATER

DESCRIPTION

Veterinary 5% dextrose in 0.9% Sodium Chloride Injection, USP is a sterile, non-pyrogenic solution for fluid replenishment in single dose containers for intravenous administration. Discard unused portion. It contains no antimicrobial agents.

Table 1. Veterinary 5% Dextrose in 9% Sodium Chloride Injection, USP
Size (mL) | Composition (g/ 100mL) |  | *Osmolarity (mOsmol/L) (Calculated) | pH | Concentration (mEq/L) |  | Caloric Content (kcal/L)
Size (mL) | Dextrose 1H2O | Sodium Chloride, USP (NaCl) | *Osmolarity (mOsmol/L) (Calculated) | pH | Sodium | Chloride | Caloric Content (kcal/L)
100 | 5.5 | 0.9 | 586 | 3.2-6.5 | 154 | 154 | 170
250 | 5.5 | 0.9 | 586 | 3.2-6.5 | 154 | 154 | 170
500 | 5.5 | 0.9 | 586 | 3.2-6.5 | 154 | 154 | 170
1000 | 5.5 | 0.9 | 586 | 3.2-6.5 | 154 | 154 | 170

No venting is necessary during infusion.

CLINICAL PHARMACOLOGY

Veterinary 5% Dextrose in 0.9% Sodium Chloride Injection, USP has value as a source of water, electrolytes. It is capable of inducing diuresis depending on the clinical condition of the patient.

INDICATIONS AND USAGE

Veterinary 5% Dextrose in 0.9% Sodium Chloride, USP is indicated as a source of water, electroytes and calories.

CONTRAINDICATIONS

Solutions containing 5% Dextrose in 0.9% Sodium Chloride Injection, USP may be contraindicated in patients with known allergy to corn or corn products.

WARNINGS

Excessive administration of 5% Dextrose in 0.9% Sodium Chloride Injection, USP may result in significant hypokalemia.

Veterinary 5% Dextrose in 0.9% Sodium Chloride Injection, USP, should be used with great care, if at all, in patients with congestive heart failure, severe renal insufficiency, and in clinical states in which there exists edema with sodium retention.

Veterinary 5% Dextrose in 0.9% Sodium Chloride Injection, USP should not be administered simultaneously with blood through the same administration set because of the possibility of pseudo agglutination or hemolysis.

The container label for these injections bears the statement: Do not administer simultaneously with blood.

The intravenous administration of veterinary 5% Dextrose in 0.9% Sodium Chloride Injection, USP can cause fluid and/or solute overloading resulting in dilution of serum electrolyte concentrations, over-hydration, congested states, or pulmonary edema.

The risk of dilutive states is inversely proportional to the electrolyte concentration of the injections.

The risk of solute overload causing congested states with peripheral and pulmonary edema is directly proportional to the electrolyte concentrations of the injections.

In patients with diminished renal function, administration of veterinary 5% Dextrose in 0.9% Sodium Chloride Injection, USP may result in sodium retention proportional to the electrolyte concentrations of the injections.

Keep out of the reach of children.

ADVERSE REACTIONS

Reactions which may occur because of the solution or the technique of administration include febrile response, infection at the site of injection, venous thrombosis or phlebitis extending from the site of injection, extravasation and hypervolemia.

If an adverse reaction does occur, discontinue the infusion, evaluate the patient, institute appropriate therapeutic countermeasures and save the remainder of the fluid for examination if deemed necessary.

PRECAUTIONS

5% Dextrose in 0.9% Sodium Chloride Injection, USP should be used with caution in patients with overt or subclinical diabetes mellitus.

Clinical evaluation and periodic laboratory determinations are necessary to monitor changes in fluid balance, electrolyte concentrations, and acid base balance during prolonged parenteral therapy or whenever the condition of the patient warrants such evaluation.

Caution must be exercised in the administration of veterinary 5% Dextrose in 0.9% Sodium Chloride Injection, USP to patients receiving corticosteroids or corticotrophin.

Veterinary 5% Dextrose in 0.9% Sodium Chloride Injection, USP should be used with caution in patients with known subclinical or overt diabetes mellitus.

Do not administer unless solution is clear and both seal and container are intact.

DOSAGE AND ADMINISTRATION

As directed by a veterinarian. Dosage is dependent upon the age, weight and clinical condition of the patient, as well as laboratory determinations.

Parenteral drug products should be inspected visually for particulate matter and discolorations prior to administration whenever solution and container permit.

All injections in plastic containers are intended for intravenous administration using sterile equipment.

Additives may be incompatible. Complete information is not available. Those additives known to be incompatible should not be used. Consult with pharmacist, if available. If, in the informed judgment of the veterinarian, it is deemed advisable to introduce additives, use aseptic technique. Mix thoroughly when additives have been introduced.

Do not store solutions containing additives. Discard unused portion.

OVERDOSAGE

In an event of over hydration or solute overload, re-evaluate the patient and institute appropriate corrective measures. See Warnings, Precautions and Adverse Reactions.

STORAGE

Store below 30ºC (86ºF).

PRECAUTION FOR USE OF THE BOTTLE

This is a single dose container and does not contain preservatives. If leaks are found, discard solution as sterility may be impaired.

Use the solution immediately after the bottle is opened, discard the remaining one. Discard unused portion. If supplemental medication is desired follow directions below:

Do not administer simultaneously with blood.
Do not use it unless solution is clear and seal is intact, the solution containing dextrose may be contraindicated in patients with a known allergy to corn or corn products.

Preparation and administration

Check for minute leaks by squeezing the container firmly. If leaks are found, discard solution as sterility may be impaired.
Suspend container from eyelet support.
Remove Plastic protector from ports area at the bottom of container.
Hold the bottle in vertical position and inset pyrogen free IV administration set in the outlet port. Use aseptic Technique.

To add medication

WARNING:Additives may be incompatible.

To add medication before solution administration

1. Prepare medication site.

2. Using syringe with 19 to 22 gauge needle, puncture inlet port and inject.

3. Mix solution and medication thoroughly. Return container to in-use position and continue administration. For high density medication such as potassium chloride, squeeze ports while ports are upright and mix thoroughly.

To add medication during solution administration

1. Close clamp on the set.

2. Prepare medication site.

3. Using syringe with 19 to 22 gauge needle, puncture inlet port and inject.

4. Remove container from IV pole and/or turn to an upright position.

5. Mix solution and medication thoroughly.

6. Return container to in use position and continue administration.

CAUTION: Federal law (USA) restricts this drug to use by or on the order of a licensed veterinarian.

PACKAGE INSERT

For Animal Use Only

Dextrose 5% in 0.9% sodium chloride (Bottles)

Dextrose 5% in 0.9% Sodium Chloride Injection, USP

For Veterinary Use Only

Dextrose 5% in 0.9% Sodium Chloride 100 mL NDC 72483-205-01

Dextrose 5% in 0.9% Sodium Chloride 250 mL NDC 72483-205-25

Dextrose 5% in 0.9% Sodium Chloride 500 mL NDC 72483-205-05

Dextrose 5% in 0.9% Sodium Chloride 1000 mL NDC 72483-205-10

Dextrose 5% in 0.9% sodium chloride (Bags)

Dextrose 5% in 0.9% Sodium Chloride Injection, USP

For Veterinary Use Only

Dextrose 5% in 0.9% Sodium Chloride 100 mL NDC 72483-205-08

Dextrose 5% in 0.9% Sodium Chloride 250 mL NDC 72483-205-07

Dextrose 5% in 0.9% Sodium Chloride 500 mL NDC 72483-205-06

Dextrose 5% in 0.9% Sodium Chloride 1000 mL NDC 72483-205-04

Dextrose 5% in 0.9% Sodium Chloride 3000 mL NDC 72483-205-03

Dextrose 5% in 0.9% Sodium Chloride 5000 mL NDC 72483-205-02